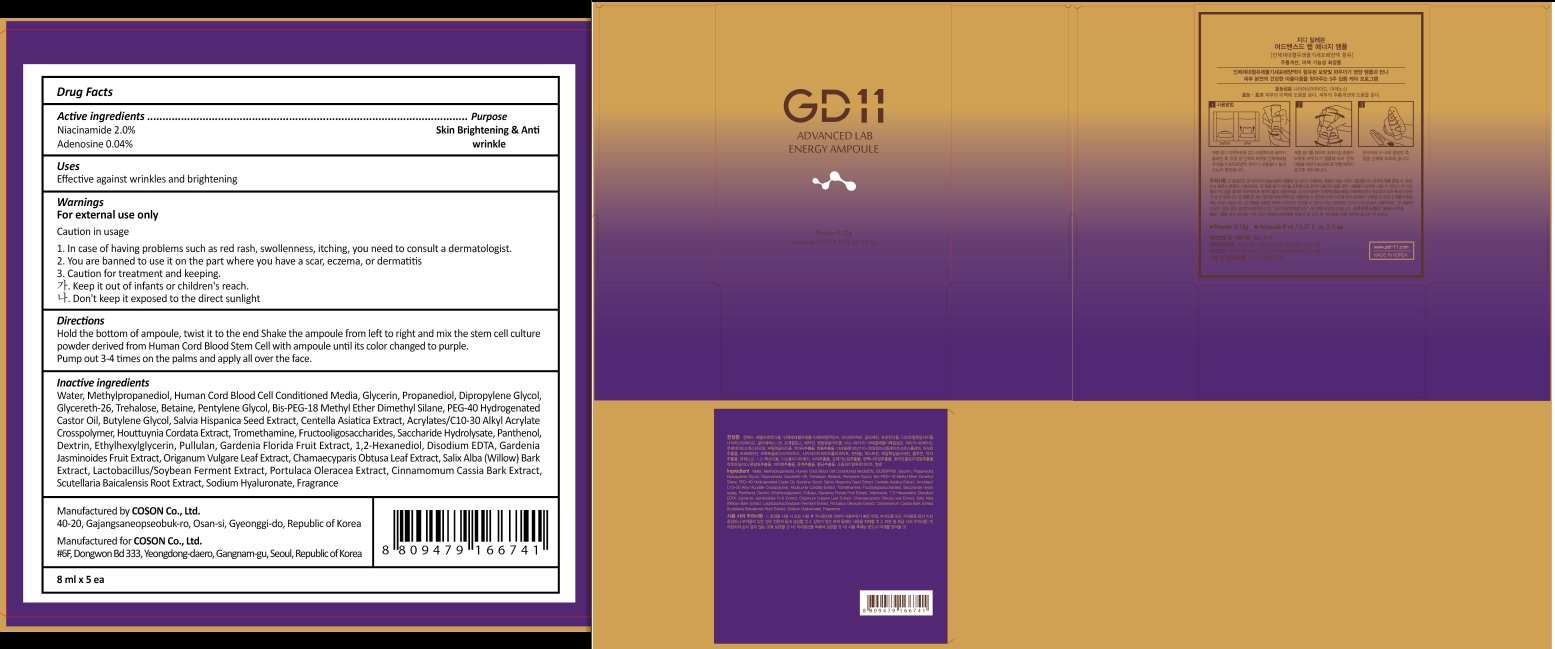 DRUG LABEL: GD11 ADVANCED LAB ENERGY AMPOULE
NDC: 62171-080 | Form: LIQUID
Manufacturer: Coson Co., Ltd.
Category: otc | Type: HUMAN OTC DRUG LABEL
Date: 20170824

ACTIVE INGREDIENTS: Niacinamide 0.16 g/8 mL; Adenosine 0.003 g/8 mL
INACTIVE INGREDIENTS: Water; Methylpropanediol

ACTIVE INGREDIENT

Active ingredients: Niacinamide 2.0%, Adenosine 0.04%

INACTIVE INGREDIENT

Inactive ingredients: Water, Methylpropanediol, Human Cord Blood Cell Conditioned Media, Glycerin, Propanediol, Dipropylene Glycol, Glycereth-26, Trehalose, Betaine, Pentylene Glycol, Bis-PEG-18 Methyl Ether Dimethyl Silane, PEG-40 Hydrogenated Castor Oil, Butylene Glycol, Salvia Hispanica Seed Extract, Centella Asiatica Extract, Acrylates/C10-30 Alkyl Acrylate Crosspolymer, Houttuynia Cordata Extract, Tromethamine, Fructooligosaccharides,Saccharide Hydrolysate,Panthenol,Dextrin,Ethylhexylglycerin,Pullulan,Gardenia Florida Fruit Extract, 1,2-Hexanediol,Disodium EDTA, Gardenia Jasminoides Fruit Extract, Origanum Vulgare Leaf Extract, Chamaecyparis Obtusa Leaf Extract, Salix Alba (Willow) Bark Extract, Lactobacillus/Soybean Ferment Extract, Portulaca Oleracea Extract, Cinnamomum Cassia Bark Extract, Scutellaria Baicalensis Root Extract, Sodium Hyaluronate, Fragrance

PURPOSE

Purpose: Skin Brightening & Anti wrinkle

WARNINGS

Warnings: For external use only

Caution in usage 1. In case of having problems such as red rash, swollenness, itching, you need to consult a dermatologist. 2. You are banned to use it on the part where you have a scar, eczema, or dermatitis 3. Caution for treatment and keeping. - Keep it out of infants or children's reach. - Don't keep it exposed to the direct sunlight

KEEP OUT OF REACH OF CHILDREN

Keep it out of infants or children's reach.

Uses

Uses: Effective against wrinkles and brightening

Directions

Directions: Hold the bottom of ampoule, twist it to the end Shake the ampoule from left to right and mix the stem cell culture powder derived from Human Cord Blood Stem Cell with ampoule until its color changed to purple. Pump out 3-4 times on the palms and apply all over the face.